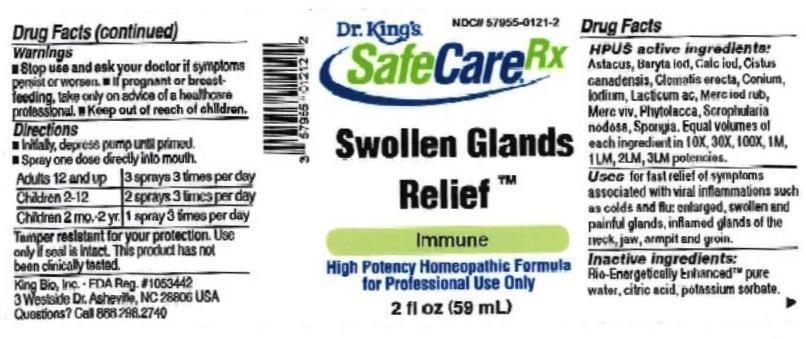 DRUG LABEL: Swollen Glands Relief
NDC: 57955-0121 | Form: LIQUID
Manufacturer: King Bio Inc.
Category: homeopathic | Type: HUMAN OTC DRUG LABEL
Date: 20161213

ACTIVE INGREDIENTS: ASTACUS ASTACUS 10 [hp_X]/59 mL; BARIUM IODIDE 10 [hp_X]/59 mL; CALCIUM IODIDE 10 [hp_X]/59 mL; HELIANTHEMUM CANADENSE 10 [hp_X]/59 mL; CLEMATIS RECTA FLOWERING TOP 10 [hp_X]/59 mL; CONIUM MACULATUM FLOWERING TOP 10 [hp_X]/59 mL; IODINE 10 [hp_X]/59 mL; LACTIC ACID, DL- 10 [hp_X]/59 mL; MERCURIC IODIDE 10 [hp_X]/59 mL; MERCURY 10 [hp_X]/59 mL; PHYTOLACCA AMERICANA ROOT 10 [hp_X]/59 mL; SCROPHULARIA NODOSA 10 [hp_X]/59 mL; SPONGIA OFFICINALIS SKELETON, ROASTED 10 [hp_X]/59 mL
INACTIVE INGREDIENTS: WATER; ANHYDROUS CITRIC ACID; POTASSIUM SORBATE

Swollen Glands Relief™

ACTIVE INGREDIENT

Drug Facts__________________________________________________________________________________________________________

HPUS active ingredients: Astacus fluviatilis, Baryta iodata, Calcarea iodata, Cistus canadensis, Clematis erecta, Conium maculatum, Iodium, Lacticum acidum, Mercurius iodatus ruber, Mercurius vivus, Phytolacca decandra, Scrophularia nodosa, Spongia tosta. Equal volumes of each ingredient in 10X, 30X, 100X, 1M, 1LM, 2LM, 3LM potencies.

INDICATIONS AND USAGE

Uses for fast relief of symptoms associated with viral inflammations such as colds and flu: enlarged, swollen and painful glands, inflamed glands of the neck, jaw, armpit, and groin.

Inactive Ingredients:

Bio-Energetically Enhanced™ pure water, citric acid and potassium sorbate.

Warnings

- Stop use and ask your doctor if symptoms persist or worsen.
- If pregnant or breast-feeding, take only on advice of a healthcare professional.

- Keep out of reach of children.

Directions

- Initially, depress pump until primed.
- Spray one dose directly into mouth.
- Adults: 3 sprays 3 times per day.
- Children 2-12 years: 2 sprays 3 times per day.
- Children 2 mo-2 yr. 1 spray 3 times per day.

OTHER SAFETY INFORMATION

Tamper resistant for your protection. Use only if safety seal is intact. This product has not been clinically tested.

PURPOSE

Uses for fast relief of symptoms associated with viral inflammations such as colds and flu:

- enlarged swollen and painful glands
- inflamed glands of the neck, jaw, armpit, and groin